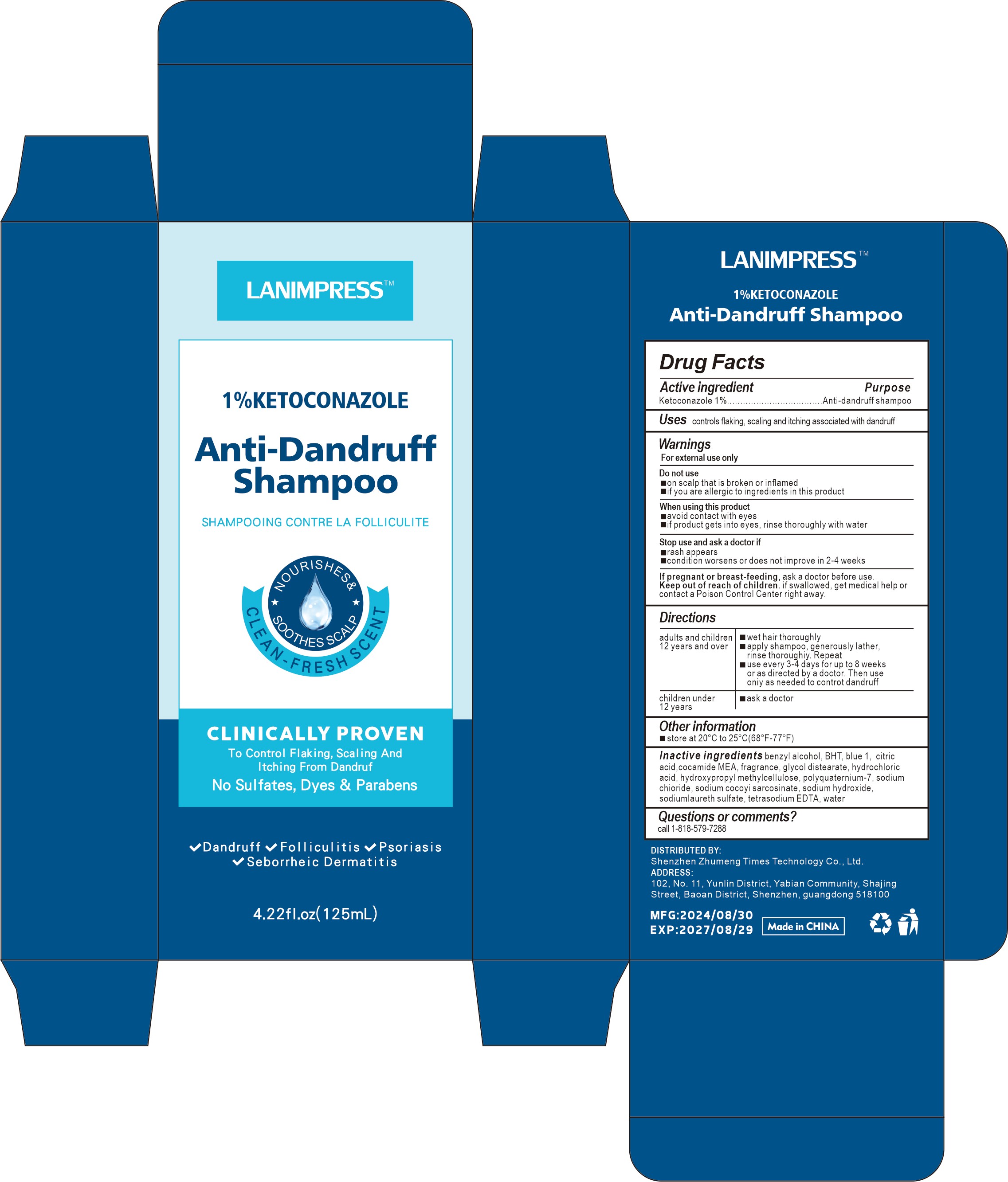 DRUG LABEL: lanimpress1%ketoconazoleantidandruffshampoo
NDC: 84372-042 | Form: LOTION
Manufacturer: Shenzhen Zhumeng Times Technology Co., Ltd.
Category: otc | Type: HUMAN OTC DRUG LABEL
Date: 20240902

ACTIVE INGREDIENTS: KETOCONAZOLE 5 g/125 mL
INACTIVE INGREDIENTS: POLYQUATERNIUM-7 (70/30 ACRYLAMIDE/DADMAC; 1600 KD); TROLAMINE; EDETATE SODIUM; HYALURONATE SODIUM; SODIUM COCOYL SARCOSINATE; FD&C BLUE NO. 1; SODIUM CHLORIDE; SODIUM LAURETH SULFATE; WATER; IVERMECTIN; METHYLPARABEN; 8-PENTADECANONE; HYDROCHLORIC ACID; BUTYLATED HYDROXYTOLUENE; GLYCOL DISTEARATE; HYPROMELLOSES; COCO MONOETHANOLAMIDE; SODIUM HYDROXIDE; ACONITIC ACID; FRAGRANCE 13576; BENZYL ALCOHOL; EDETATE DISODIUM

Active ingredients

Ketoconazole 1% Anti-dandruff shampoo

Purpose

controls flaking, scaling and itching associated with dandruff

Uses

wet hair thoroughly

apply shampoo, generously lather,rinse thoroughiy. Repeat

use every 3-4 days for up to 8 weeks or as directed by a doctor. Then use oniy as needed to controt dandruff

Warnings

For external use only

Do not use

on scalp that is broken or inflamed

if you are allergic to ingredients in this product

Dosage and administration

For external use only.

Do not use

Stop use and ask a doctor if rash occurs

When using section

rash appears

condition worsens or does not improve in 2-4 weeks.

stop use

Do not use

on scalp that is broken or inflamed

if you are allergic to ingredients in this product

Keep out of reach of children.lf swallowed, get medical help or contacta Poison Control Center right away.

Inactive ingredients

benzyl alcohol, BHT, blue 1, citric acid,cocamide MEA, fragrance, glycol distearate, hydrochloricacid, hydroxypropyl methylcellulose, polyquaternium-7, sodium chioride, sodium cocoyi sarcosinate, sodium hydroxide, sodiumlaureth sulfate, tetrasodium EDTA, waterCAPRYLATE,CARBOMER,METHYLPARABEN,TRIETHANOLAMINE,SODIUM HYALURONATE,DISODIUM EDTA，water